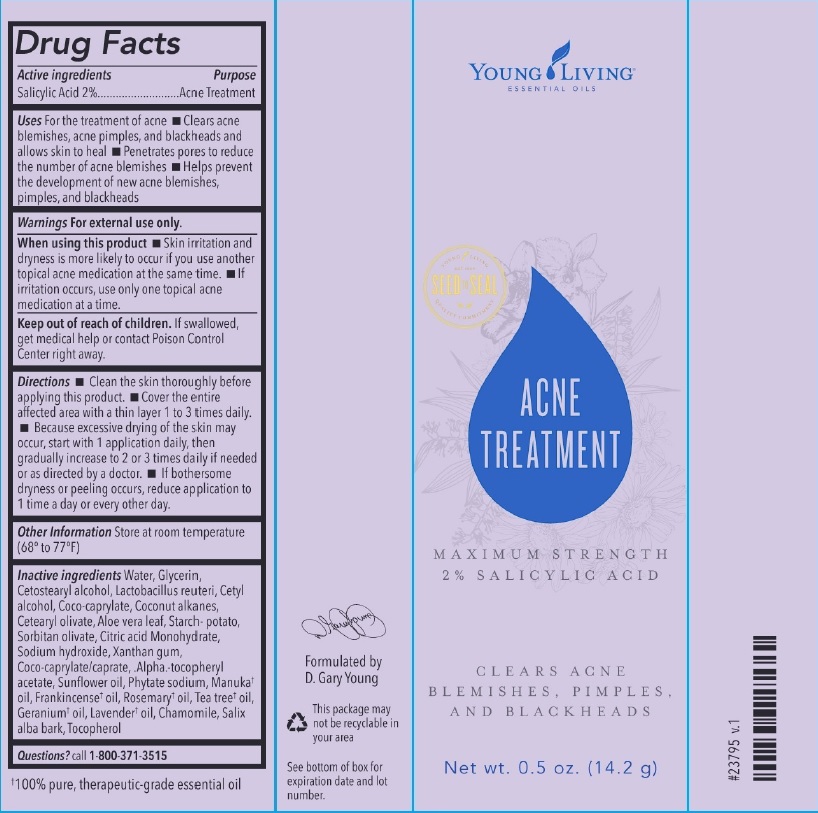 DRUG LABEL: Acne Treatment Maximum Strength
NDC: 70631-358 | Form: GEL
Manufacturer: Young Living Essential Oils, LC
Category: otc | Type: HUMAN OTC DRUG LABEL
Date: 20241204

ACTIVE INGREDIENTS: SALICYLIC ACID 2 g/100 g
INACTIVE INGREDIENTS: ALOE VERA LEAF; CETOSTEARYL ALCOHOL; CETEARYL OLIVATE; CETYL ALCOHOL; MATRICARIA CHAMOMILLA; CITRIC ACID MONOHYDRATE; COCO-CAPRYLATE; COCO-CAPRYLATE/CAPRATE; COCONUT ALKANES; .ALPHA.-TOCOPHEROL ACETATE, D-; GLYCERIN; SUNFLOWER OIL; LACTOBACILLUS REUTERI; STARCH, POTATO; WILLOW BARK; SODIUM HYDROXIDE; HEXASODIUM PHYTATE; SORBITAN OLIVATE; WATER; XANTHAN GUM; MANUKA OIL; LAVENDER OIL; FRANKINCENSE OIL; ROSEMARY OIL; TEA TREE OIL; GERANIUM OIL, ALGERIAN TYPE

Young Living Acne Treatment

Active Ingredients

Salicylic Acid 2%

Purpose

Acne Treatmen

Uses

For the treatment of acne

- Clears acne blemishes, acne pimples, and blackheads and allows skin to heal
- Penetrates pores to reduce the number of acne blemishes
- Helps prevent the developent of new acne blemishes, pimples and blackheads.

Warnings For external use only

When using this Product

- Skin irritation and dryness is more likely to occur if you use another topical acne medication at the same time

- If irritation occurs, use only one topical acne medication at a time

Keep out of reach of children.

If swallowed, get medical help or contact Poison Control Center right away.

Directions

- Clean the skin thuroughly before applying this product
- Cover the entire affected area with a thin layer 1 to 3 times daily
- Because excessive drying of the skin may occur, start with 1 application daily, then gradually increase to 2 to 3 times daily if needed or as directed by a doctor.
- If bothersome dryness of peeling occurs, reduce application to 1 time a day or every other day.

Other Information

Store at room temperature (68° to 77°F)

Inactive Ingredients

Water, Glycerin, Cetostearyl alcohol, Lactobacillus reuteri, Cetyl alcohol, Coco-caprylate, Coconut alkanes, Cetearyl olicate, Aloe vera leaf, Starch-potato, Sorbitan olivate, Citric acid Monohydrate, Sodium hydroxide, Xanthan gum, coco-caprylate/caprate, .Alpha.-tocopheryl acetate, Sunflower oil, Phylate sodium, Manuka oil, Frankincense oil, Rosemary oil, Tea tree Oil, Geranium oil, Lavender oil, Chamomile, Salix alba bark, Tocopherol